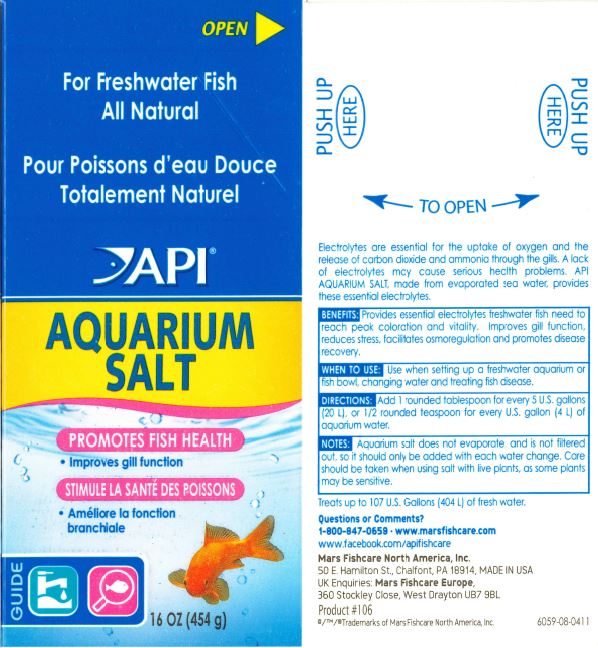 DRUG LABEL: API AQUARIUM SALT
NDC: 17163-106 | Form: GRANULE, FOR SOLUTION
Manufacturer: MARS FISHCARE NORTH AMERICA, INC.
Category: animal | Type: OTC ANIMAL DRUG LABEL
Date: 20240814

ACTIVE INGREDIENTS: SODIUM CHLORIDE 100 g/100 g

Drug Label

DESCRIPTION

Electrolytes are essential for the uptake of oxygen and the release of carbon dioxide and ammonia through the gills. A lack of electrolytes may cause serious health problems. API AQUARIUM SALT, made from evaporated sea water, provides these essential electrolytes.

BENEFITS:

Provides essential electrolytes freshwater fish need to reach peak coloration and vitality.

Improves gill function, reduces stress, facilitates osmoregulation and promotes disease recovery.

INDICATIONS AND USAGE

WHEN TO USE:

Use when setting up a freshwater aquarium or fish bowl, changing water and treating fish disease.

DIRECTIONS:

Add 1 rounded tablespoon for every 5 U.S. gallons (20 L) or 1/2 rounded teaspoon for every U.S. (4 L) of aquarium water.

USER SAFETY WARNINGS

NOTES:

Aquarium salt does not evaporate and is not filtered out, so it should only be added with each water change.

Care should be taken when using salt with live plants, as some plants may be sensitive.

Treats up to 107 U.S. Gallons (404 L) of fresh water.

Questions or Comments?

1-800-847-0659

www.marsfishcare.com

www.facebook.com/apifishcare

PACKAGE LABEL

OPEN

For Freshwater Fish

All Natural

API

AQUARIUM

SALT

PROMOTES FISH HEALTH

Improves gill function

GUIDE

16 OZ (454g)